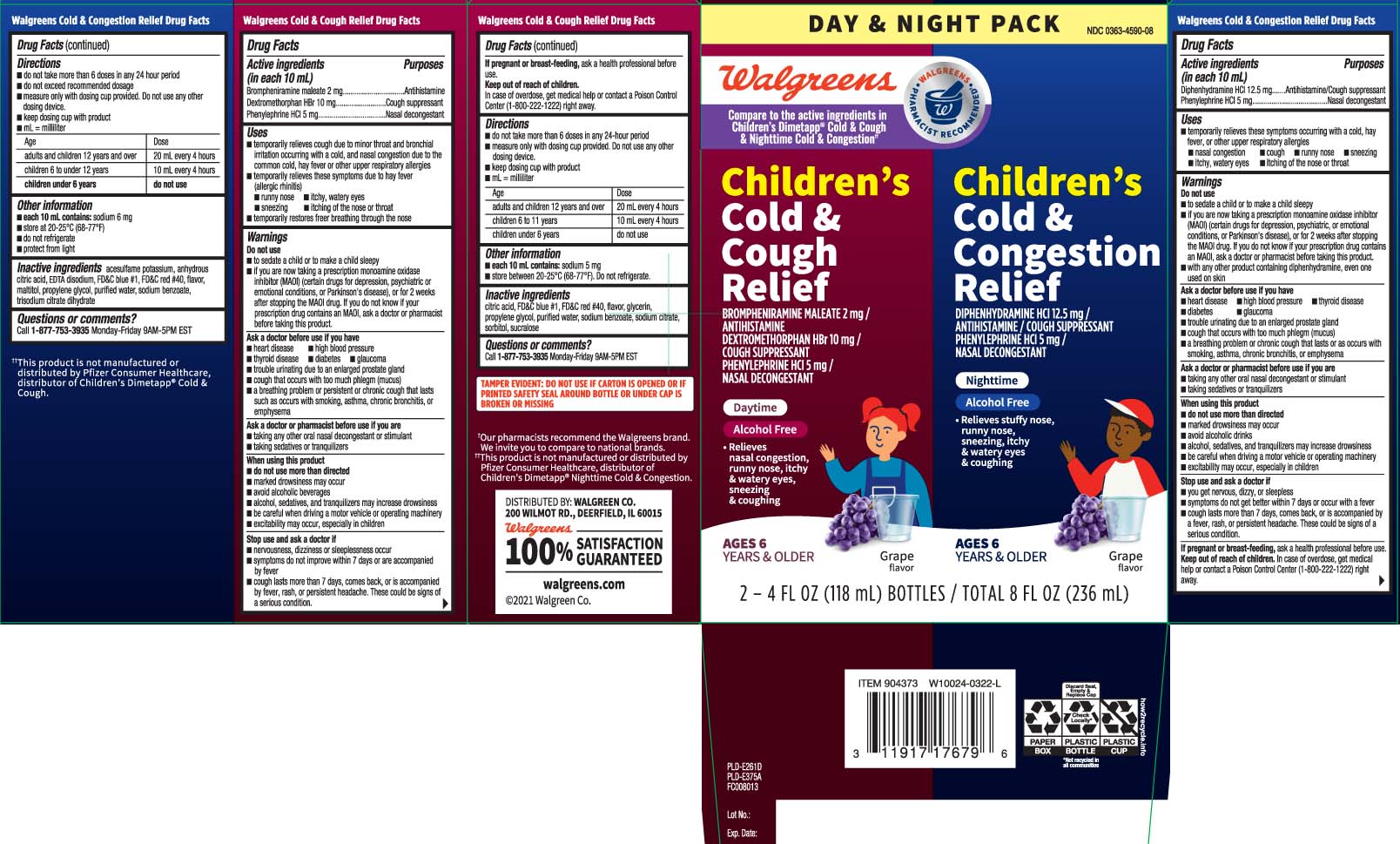 DRUG LABEL: Daytime Cold and Cough and NightTime Cold and Congestion
NDC: 0363-4590 | Form: KIT | Route: ORAL
Manufacturer: Walgreens
Category: otc | Type: HUMAN OTC DRUG LABEL
Date: 20240621

ACTIVE INGREDIENTS: DIPHENHYDRAMINE HYDROCHLORIDE 12.5 mg/10 mL; PHENYLEPHRINE HYDROCHLORIDE 5 mg/10 mL; BROMPHENIRAMINE MALEATE 2 mg/10 mL; DEXTROMETHORPHAN HYDROBROMIDE 10 mg/10 mL; PHENYLEPHRINE HYDROCHLORIDE 5 mg/10 mL
INACTIVE INGREDIENTS: FD&C BLUE NO. 1; PROPYLENE GLYCOL; WATER; FD&C RED NO. 40; ACESULFAME POTASSIUM; ANHYDROUS CITRIC ACID; EDETATE DISODIUM; MALTITOL; SODIUM BENZOATE; TRISODIUM CITRATE DIHYDRATE; GLYCERIN; PROPYLENE GLYCOL; WATER; SORBITOL; ANHYDROUS CITRIC ACID; FD&C BLUE NO. 1; FD&C RED NO. 40; SODIUM BENZOATE; SUCRALOSE; TRISODIUM CITRATE DIHYDRATE

DRUG FACTS

Active ingredients for Nighttime (in each 10 mL)

Diphenhydramine HCI 12.5 mg

Phenylephrine HCI 5 mg

Active ingredients for Daytime (in each 10 mL)

Brompheniramine Maleate 2 mg

Dextromethorphan HBr 10mg

Phenylephrine HCl 5 mg

Purpose for Nighttime

Antihistamine / Cough suppressant

Nasal Decongestant

Purpose for Daytime

Antihistamine

Cough suppressant

Nasal decongestant

Uses

Nighttime

- temporarily relieves these symptoms occuring with a cold, hay fever, or other upper respiratory allergies

- nasal congestion
- cough
- runny nose
- sneezing
- itchy, watery eyes
- itching of the nose or throat

Daytime

- temporaily relieves cough due to minor throat and bronchial irritation occuring with a cold, and nasal congestion due to the common cold, hay fever or other upper respiratory allergies
- temporarily relieves these symptoms due to hay fever (allergic rhinitis)
  - runny nose
  - itchy, watery eyes
  - sneezing
  - itching of the nose or throat
- temporarily restores freer breathing through the nose

Warnings

Do not use

Nighttime

- to sedate a child or to make a child sleepy.
- if you are now taking a prescription monoamine oxidase inhibitor (MAOI) (certain drugs for depression, psychiatric or emotional conditions, or Parkinson’s disease), or for 2 weeks after stopping the MAOI drug. If you do not know if your prescription drug contains an MAOI, ask a doctor or pharmacist before taking this product
- with any other product containing diphenhydramine, even one used on skin.

Daytime

- to sedate a child or to make sleepy
- if you are now taking a prescription monoamine oxidase inhibitor (MAOI)(certain drugs for depression,psychiatic or emotional conditions, or Parkinson's disease), or for 2 weeks after stopping the MAOI drug. If you do not know if your prescription drug contains an MAOI, ask a doctor or pharmacist before taking this product.

Ask a doctor before use if you have

Nighttime

- heart disease
- high blood pressure
- thyroid disease
- diabetes
- glaucoma
- trouble urinating due to an enlarged prostate gland
- cough that occurs with too much phlegm (mucus)
- a breathing problem or chronic cough that last as occurs with smoking,asthma, chronic bronchitis or emphysema

Daytime

- heart disease
- high blood pressure
- thyroid disease
- diabetes
- glaucoma
- trouble urinating due to an enlarged gland
- cough that occurs with too much phlegm (mucus)
- a breathing problem or persistent or chronic cough that lasts such as occurs with smoking, asthma, chronic bronchitis or emphysema

Ask a doctor or pharmacist before use if you are

Nighttime

- taking any other oral nasal decongestant or stimulant
- taking sedative or tranquilizers

Daytime

- taking any other oral nasal decongestant or stimulant
- taking sedative or tranquilizers

When using these products

Nighttime

- do not use more than directed
- marked drowsiness may occur
- avoid alcoholic drinks
- alcohol, sedatives and tranquilizers may increase drowsiness
- be careful when driving a motor vehicle or operating machinery
- excitablity may occur, especially in children

Daytime

- do not use more than directed
- marked drowsiness may occur
- avoid alcoholic drinks
- alcohol, sedative and tranquilizers may increase drowsiness
- be careful when driving a motor vehicle or operating machinery
- excitability may occur, especially in children

Stop use and ask a doctor if

Nighttime

- you get nervous, dizzy or sleepless
- symptoms do not get better within 7 days or occur with a fever
- cough lasts more than 7 days, comes back, or is accompanied by fever, rash, or persistent headache. These could be signs of a serious condition

Daytime

- nervousness, dizziness or sleeplessness occur
- symptoms do not improve within 7 days or are accompanied by fever
- cough lasts more than 7 days, comes back or is accompanied by fever, rash, or persistent headache. These could be signs of a serious condition

If pregnant or breast-feeding,

Nighttime

ask a health professional before use.

Daytime

ask a health professional before use

Keep out of reach of children.

Nighttime

In case of overdose, get medical help or contact a Poison Control Center (1-800-222-1222) right away.

Daytime

In case of overdose, get medical help or contact a Poison Control Center (1-800-222-1222) right away.

Directions

Nighttime

- do not take more than 6 doses in any 24 hours period
- do not exceed recommended dosage
- measure only with dosing cup provided. Do not use any other dosing device
- keep dosing cup with product
- mL = mililiter

Age | Dose
adults and children 12 years and over | 20 mL every 4 hours
childen 6 to under 12 years | 10 mL every 4 hours
children under 6 years | do not use

Daytime

- do not take more than 6 doses in any 24 hours period
- measure only with dosing cup provided. Do not use any other dosing dosing device.
- keep dosing cup with product
- mL = mililiter

Age | Dose
adults and children12 years and over | 20 mL every 4 hours
children 6 to under 11 years | 10 mL every 4 hours
Children under 6 years | do not use

Other information

Nighttime

- each 10 mL contains: sodium 6 mg
- store at 20-25ºC (68-77ºF)
- do not refrigerate
- protect from light

Daytime

- each 10 mL contains: 5 mg
- store between 20-25ºC (68-77ºF). Do not refrigerate.

Inactive ingredients

Nighttime

acesulfame potassium, anhydrous citric acid, EDTA disodium, FD&C Blue #1, FD&C red #40, flavor, maltitol, propylene glycol, purified water, sodium benzoate, trisodium citrate dihydrate

Daytime

citric acid, FD&C blue #1, FD&C red #40, flavor, glycerin, propylene glycol, purified water, sodium benzoate, sodium citrate, sorbitol, sucralose

Questions or comments?

Call 1-877-753-3935 Monday-Friday 9AM-5PM EST

Principal Display Panel

Compare to the active ingredients in Children's Dimetapp® Cold & Cough & Nighttime Cold & Congestion††

Children's Cold & Congestion Relief

DIPHENHYDRAMINE HCl 12.5 mg /

ANRIHISTAMINE / COUGH SUPPRESSANT

PHENYLEPHRINE HCl 5 mg /

NASAL DECONGESTANT

Nighttime

Alcohol Free

- Relieves stuffy nose, runny nose, sneezing, itchy & watery eyes & coughing

AGES 6 YEARS & OLDER

Grape flavor

DOSING CUP INCLUDED

AGES 6 + YEARS

TAMPER EVIDENT: DO NOT USE IF CARTON IS OPENED OR IF PRINTED SAFETY SEAL AROUND BOTTLE OR UNDER CAP IS BROKEN OR MISSING.

††This product is not manufactured or distributed by Pfizer Consumer Healthcare, distributor of Children's Dimetapp® Nighttime Cold & Congestion.

DAYTIME

Children's Cold & Cough Relief

BROMPHENIRAMINE MALEATE 2 mg

ANTIHISTAMINE

DEXTROMETHORPHAN HBr 10 mg /

COUGH SUPPRESSANT

PHENYLEPHRINE HCI 5 mg /

NASAL DECONGESTANT

Daytime

Alcohol Free

- Relieves nasal congestion, runny nose, itchy & watery eyes, sneezing & coughing

AGES 6 YEARS & OLDER

Grape flavor

FL OZ (mL)

††This product is not manufactured or distributed by Pfizer Consumer Healthcare, Distributor of Children's Dimetapp® Cold & Cough.

DISTRIBUTED BY: WALGREEN CO.

200 WILMOT RD., DEERFIELD, IL 60015

Product Label

WALGREENS Children's Cold & Congestion Relief, Children's Cold & Cough Relief